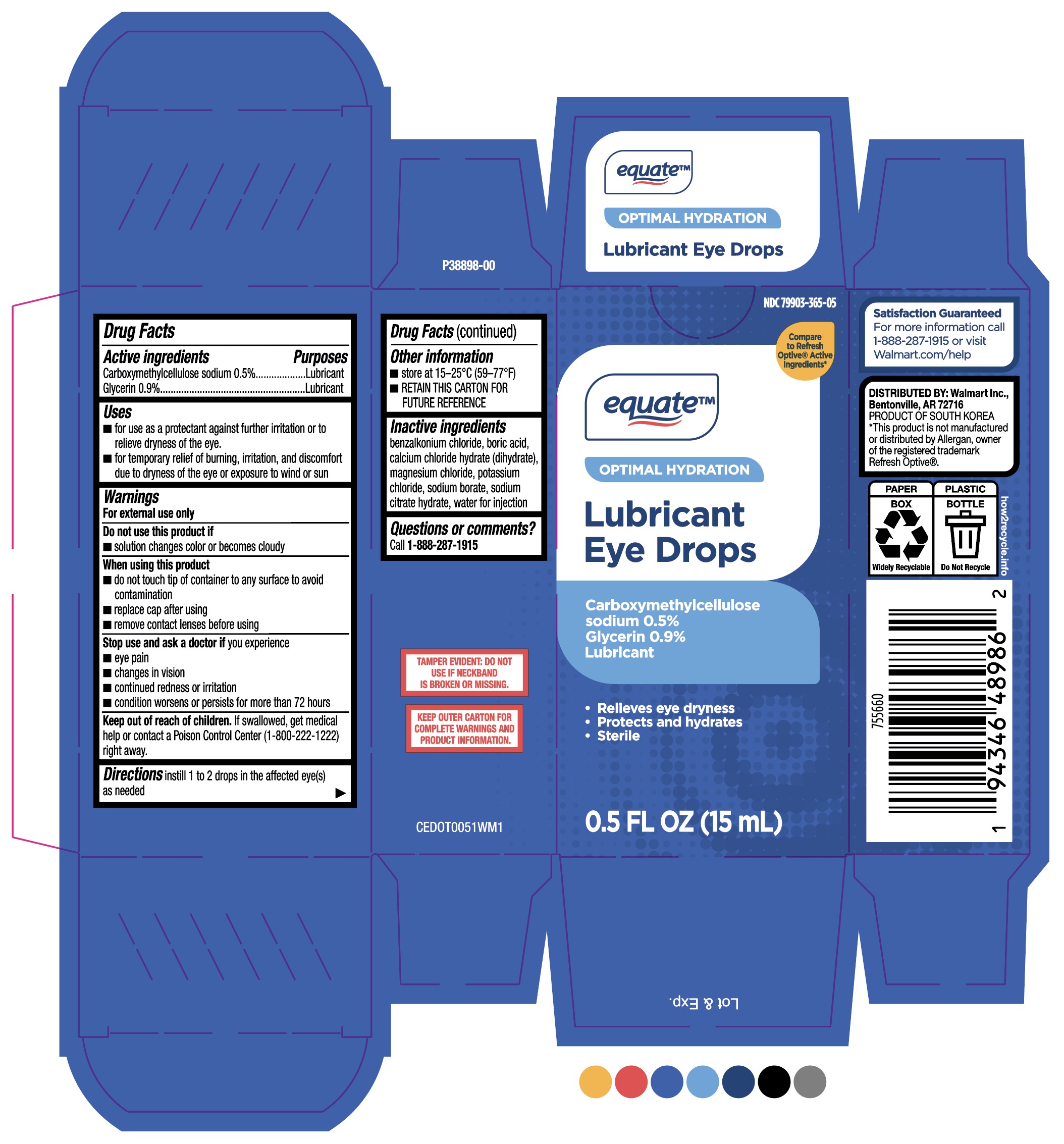 DRUG LABEL: Equate Lubricant Eye Drops
NDC: 11716-0365 | Form: SOLUTION/ DROPS
Manufacturer: Hanlim
Category: otc | Type: HUMAN OTC DRUG LABEL
Date: 20251222

ACTIVE INGREDIENTS: CARBOXYMETHYLCELLULOSE SODIUM 0.5 g/100 mL; GLYCERIN 0.9 g/100 mL
INACTIVE INGREDIENTS: CALCIUM CHLORIDE MONOHYDRATE; BORIC ACID; MAGNESIUM CHLORIDE; POTASSIUM CHLORIDE; SODIUM CITRATE MONOHYDRATE; WATER; SODIUM BORATE; BENZALKONIUM CHLORIDE

MFG (Hanlim) for Walmart (PLD) NDC 79903-365-05
Equate (Optimal Hydration) Lubricant Eye Drops

Purpose: Lubricant

Active ingredients
Carboxymethylcellulose sodium 0.5%
Glycerin 0.9%

Keep out of reach of children. If swallowed, get medical help or contact a Poison Control Center
(1-800-222-1222) right away.

Inactive Ingredients

benzalkonium chloride, boric acid, calcium chloride hydrate (dihydrate) magnesium chloride, potassium
chloride, sodium borate, sodium citrate hydrate, water for injection

DOSAGE AND ADMINISTRATION

Directions: Instill 1 to 2 drops in the affected eye(s)
as needed.

Uses
■ for use as a protectant against further irritation or to relieve dryness of the eye.
■ for temporary relief of burning, irritation, and discomfort due to dryness of the eye or exposure to wind or sun.

Warnings
For external use only
Do not use this product if
■ solution changes color or becomes cloudy
When using this product
■ do not touch lip of container to any surface to avoid contamination
■ replace cap after using
■ remove contact lenses before using
Stop use and ask a doctor if you experience
■ eye pain
■ changes in vision
■ continued redness or irritation
■ condition worsens or persists for more than72hours